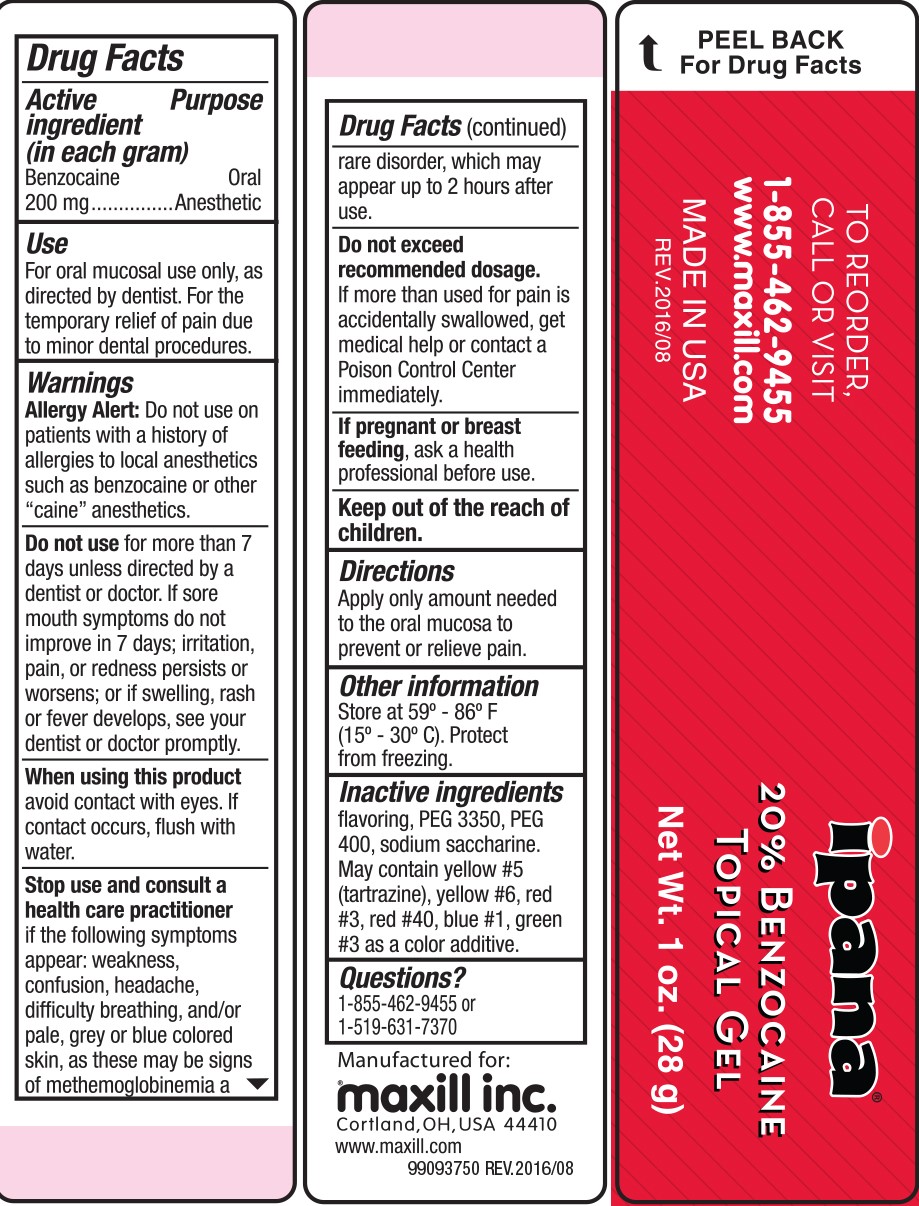 DRUG LABEL: Ipana 20% Benzocaine Topical
NDC: 69510-351 | Form: GEL
Manufacturer: Maxill Inc.
Category: otc | Type: HUMAN OTC DRUG LABEL
Date: 20251217

ACTIVE INGREDIENTS: BENZOCAINE 200 mg/1 g
INACTIVE INGREDIENTS: POLYETHYLENE GLYCOL 3350; POLYETHYLENE GLYCOL 400; SACCHARIN SODIUM; FD&C YELLOW NO. 5; FD&C YELLOW NO. 6; FD&C RED NO. 3; FD&C RED NO. 40; FD&C BLUE NO. 1; FD&C GREEN NO. 3

Ipana 20% Benzocaine Topical Bubble Gum

Active Ingredients (in each gram)

Benzocaine 200mg

Purpose

Oral Anesthetic

Use

For oral mucosal use only, as directed by dentist. For the temporary relief of pain due to minor dental procedures.

Warnings

Allergy alert: Do not use on patients with a history of allergies to local anesthetics such as benzocaine or other "caine" anesthetics.

Do not use for more than 7 days unless directed by a dentist or doctor. If sore mouth symptoms do not improve in 7 days; irritation, pain, or redness persists or worsens; or if swelling, rash or fever develops, see your dentist or doctor promptly.

When using this product avoid contact with eyes. If contact occurs, flush with water.

Stop use and consult a health care practitioner if the following symptoms appear: weakness, confusion, headache, difficulty breathing, and/or pale, grey or blue colored skin, as these may be signs of methemoglobinemia, a rare disorder, which may appear up to 2 hours after use.

Do not exceed recommended dosage. If more than used for pain is accidentally swallowed, get medical help or contact a Poison Control Center immediately.

If pregnant or breastfeeding, ask a health professional before use.

Keep out of reach of children.

Directions

Apply only amount needed to the oral mucosa to prevent or relieve pain.

Other Information

Store at 59°-86°F (15°-30°C). Protect from freezing.

Inactive Ingredients

flavoring, PEG 3350, PEG 400, sodium saccharin. May contain yellow #5 (tartrazine), yellow #6, red #3, red #40, blue #1, green #3 as a color additive.

Questions?

1-855-462-9455 or 1-519-631-7370